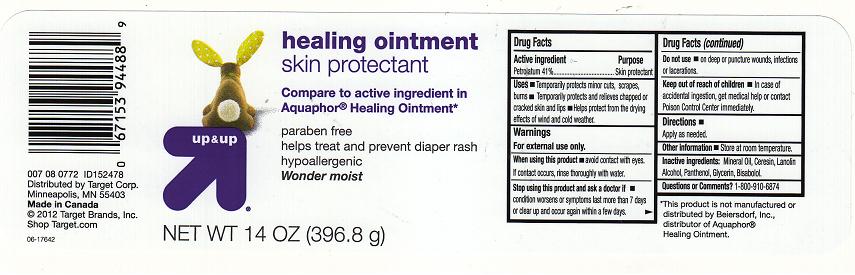 DRUG LABEL: Healing
NDC: 11673-330 | Form: JELLY
Manufacturer: TARGET CORPORATION
Category: otc | Type: HUMAN OTC DRUG LABEL
Date: 20111215

ACTIVE INGREDIENTS: PETROLATUM 41.0 g/100 g
INACTIVE INGREDIENTS: MINERAL OIL; CERESIN; LANOLIN ALCOHOLS; PANTHENOL; GLYCERIN; .ALPHA.-BISABOLOL, (+/-)-

DRUG FACTS

ACTIVE INGREDIENT

PETROLATUM 41%

PURPOSE

SKIN PROTECTANT

USES

TEMPORARILY PROTECTS MINOR CUTS, SCRAPES, BURNS. TEMPORARILY PROTECTS AND RELIEVES CHAPPED OR CRACKED SKIN AND LIPS. HELPS PROTECT FROM THE DRYING EFFECTS OF WIND AND COLD WEATHER.

WARNINGS

FOR EXTERNAL USE ONLY.

WHEN USING THIS PRODUCT

AVOID CONTACT WITH EYES. IF CONTACT OCCURS, RINSE THOROUGHLY WITH WATER.

STOP USING THIS PRODUCT AND ASK A DOCTOR IF

CONDITION WORSENS OR SYMPTOMS LAST MORE THAN 7 DAYS OR CLEAR UP AND OCCUR AGAIN WITHIN A FEW DAYS.

DO NOT USE

ON DEEP OR PUNCTURE WOUNDS, INFECTIONS OR LACERATIONS.

KEEP OUT OF REACH OF CHILDREN

IN CASE OF ACCIDENTAL INGESTION, GET MEDICAL HELP OR CONTACT POISON CONTROL CENTER IMMEDIATELY.

DIRECTIONS

APPLY AS NEEDED.

OTHER INFORMATION

STORE AT ROOM TEMPERATURE.

INACTIVE INGREDIENTS:

MINERAL OIL, CERESIN, LANOLIN ALCOHOL, PANTHENOL, GLYCERIN, BISABOLOL.

QUESTIONS OR COMMENTS?

1-800-910-6874